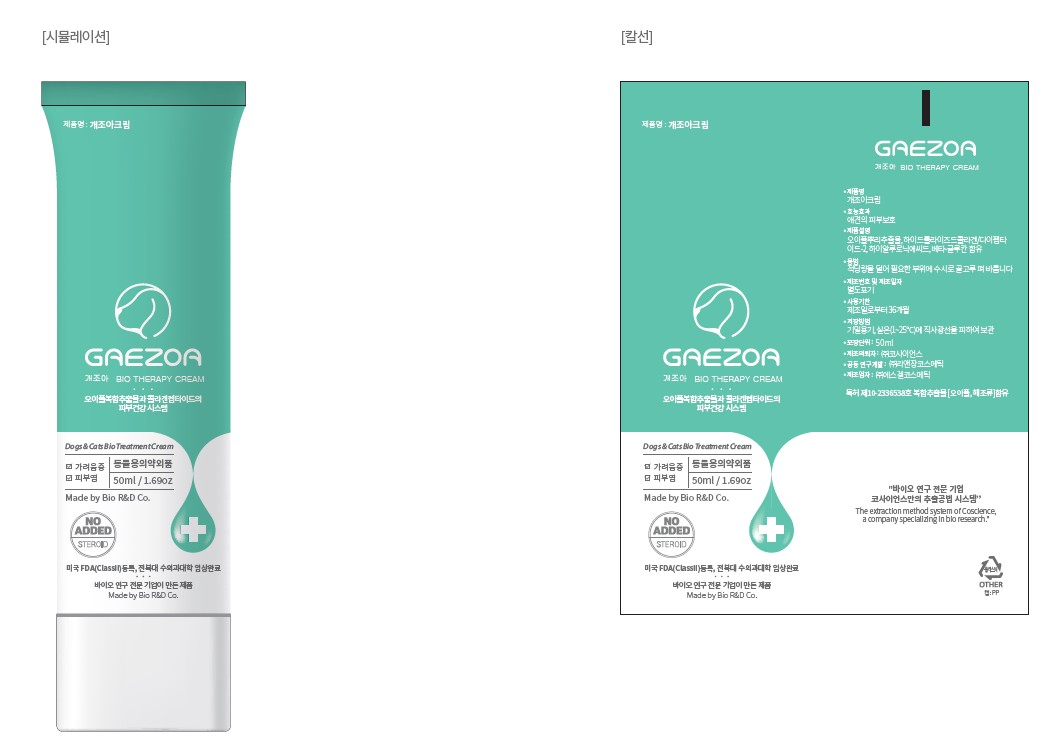 DRUG LABEL: Gaezoa Cream
NDC: 77008-6751 | Form: CREAM
Manufacturer: BIOHERB Co., Ltd.
Category: otc | Type: HUMAN OTC DRUG LABEL
Date: 20251230

ACTIVE INGREDIENTS: CAMELLIA SINENSIS LEAF 3.2 g/100 g; HYALURONIC ACID 0.64 g/100 g; GLYCERIN 16 g/100 g
INACTIVE INGREDIENTS: WATER 50.72 g/100 g

Gaezoa Cream

INDICATIONS AND USAGE

Take an appropriate amount and apply evenly to the needed areas as often as necessary

KEEP OUT OF THE REACH OF CHILDREN.

DOSAGE AND ADMINISTRATION

50mL

Warning

PURPOSE

Bio Therapy Cream

INACTIVE INGREDIENT

Water
Hyaluronic acid
Sodium Hyaluronate
Dipotassium Glycyrrhizate
Elaeagnus Glabra Extract (and)
Propanediol (and) Glycerin (and)
Dihydroxyacetophenon
Glycerin
Hydrolyzed Sclerotium Gum
Cetearyl Olivate, Sorbitan Olivate
Hydrolyzed Collagen/Dipeptide-2
Caprylic/Capric Triglyceride
Brassica Campestris (Rapeseed) Seed Oil, Polygonum Tinctorium Leaf Extract, Cocos Nucifera (Coconut) Oil, Quercus Suber Bark Extract, Oak Root Extract, Simmondsia Chinensis (Jojoba) Seed Oil (and) Avena Sativa (Oat) Kernel Oil (and) Bacillus Ferment
beta glucan
Water(and) Poterium Officinale Root Extract(and) Camellia Sinensis Leaf(and) Undaria Pinnatifida Extract (and) Laminaria Japonica Extract (and) Porphyra Tenera Extract (and) Elaeagnus Glabra Extract (and) Hydroxyacetophenone (and) Propanediol
Cordyceps Sinensis Extract, Olea Europaea (Olive) Leaf Extract,
Lactobacillus Ferment Lysate, Water
Ethylhexyl Olivate,
Sodium Acrylates Copolymer,
Polyglyceryl-4 Oleate

ACTIVE INGREDIENT

Water
Hyaluronic acid
Sodium Hyaluronate

Glycerin

RECENT MAJOR CHANGES

New product